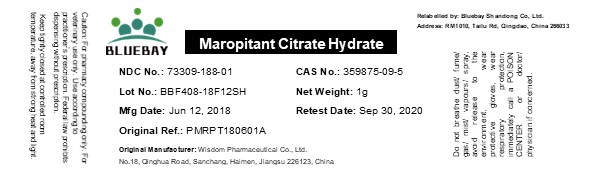 DRUG LABEL: Maropitant Citrate Hydrate
NDC: 73309-188 | Form: POWDER
Manufacturer: BLUEBAY SHANDONG CO.,LTD
Category: other | Type: BULK INGREDIENT
Date: 20200909

ACTIVE INGREDIENTS: MAROPITANT CITRATE 1 g/1 g

Maropitant Citrate Hydrate